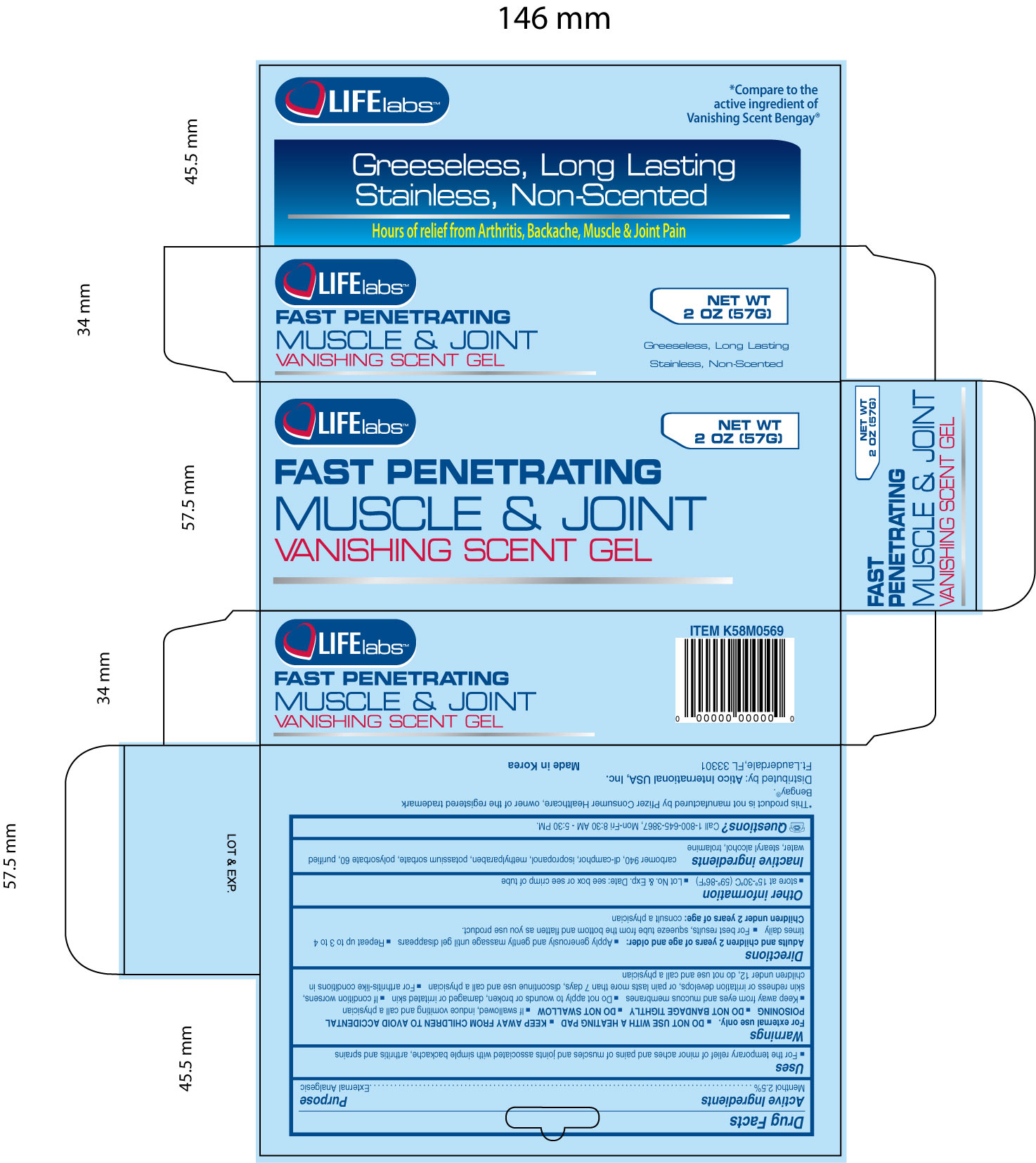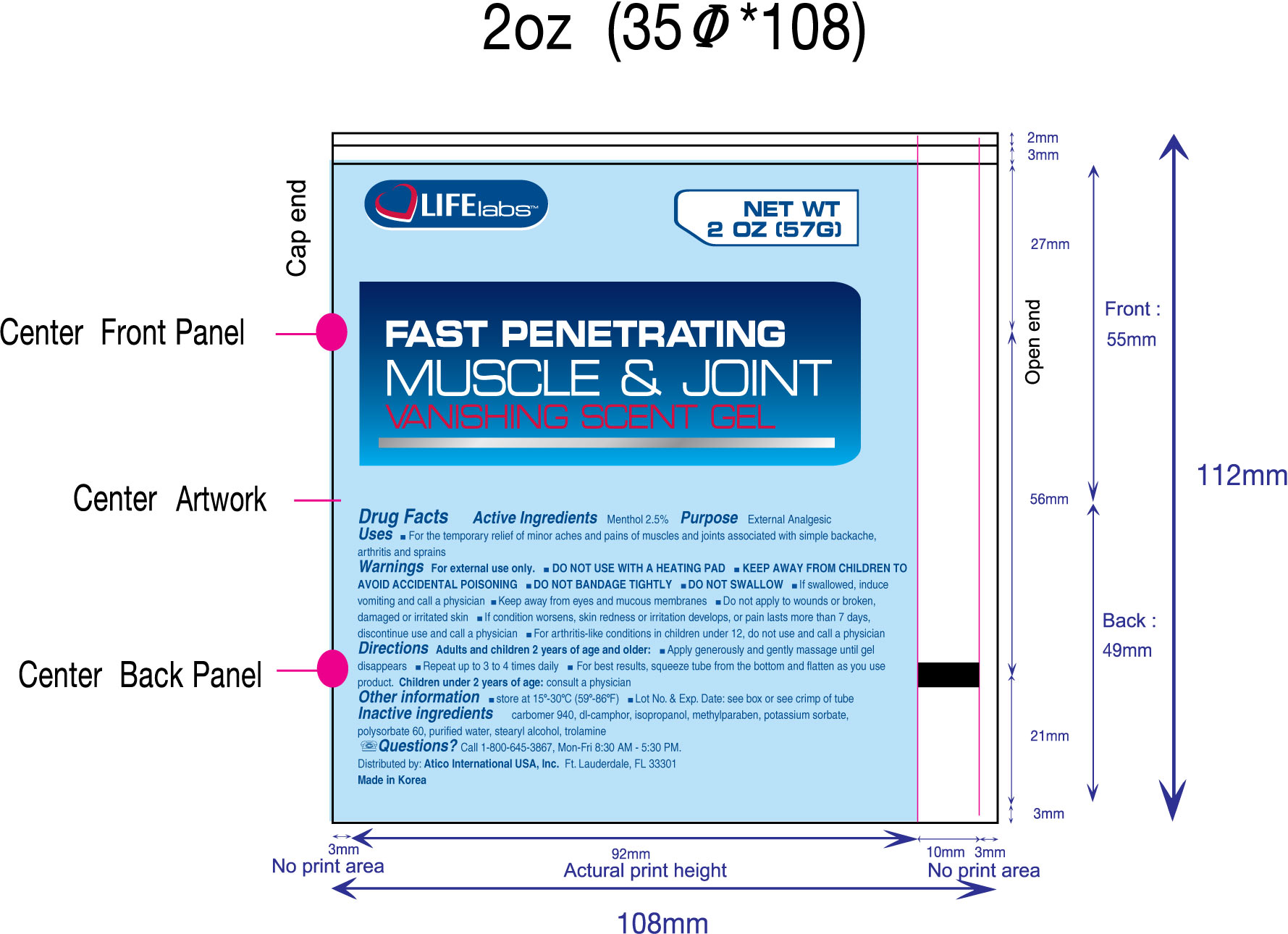 DRUG LABEL: Muscle and Joint Vanishing Scent
NDC: 51852-104 | Form: GEL
Manufacturer: LIFElabs, a Division of Atico International USA, INC.
Category: otc | Type: HUMAN OTC DRUG LABEL
Date: 20100823

ACTIVE INGREDIENTS: Menthol 25 mg/1 g
INACTIVE INGREDIENTS: Carbomer Homopolymer Type C; Isopropyl Alcohol; Methylparaben; Potassium Sorbate; Polysorbate 60; Water; Stearyl Alcohol; Trolamine; Camphor (Synthetic)

LIFElabs, a Division of Atico International USA, INC.

Muscle and Joint Vanishing Scent (Fast Penetrating)

Active Ingredients

Menthol 2.5%

Purpose

External Analgesic

Warnings

For external use only

- DO NOT USE WITH A HEATING PAD
- KEEP AWAY FROM CHILDREN TO AVOID ACCIDENTAL POISONING
- DO NOT BANDAGE TIGHTLY
- DO NOT SWALLOW
- If swallowed, induce vomiting and call a physician.
- Keep away from eyes and mucous membranes
- Do not apply to wounds or broken, damaged or irritated skin.
- If condition worsens, skin redness or irritation develops, or pain lasts more than 7 days, discontinue use and call a physician
- For arthritis-like conditions in children under 12, do not use and call a physician.

Directions

Adults and children 2 years of age and older

- Apply generously and gently massage until gel disappears
- Repeat up to 3 to 4 times daily
- For best results, squeeze tube from the bottom and flatten as you use product.

Children under 2 years of age: consult a physician

Other information

Store between 15oC - 30oC (59oF-86oF)

Lot No. and Exp. Date: see box or see crimp of tube

Inactive Ingredients

carbomer 940, dl-camphor, isopropanol, methylparaben, potassium sorbate, polysorbate 60, purified water, stearyl alcohol, trolamine

Questions?

Call 1-800-645-3867, Mon-Fri 8:30 AM - 5:30 PM.

Uses

- For the temporary relief of minor aches and pains of muscles and joints associated with simple backache, arthritis and sprains

KEEP AWAY FROM CHILDREN TO AVOID ACCIDENTAL POISONING